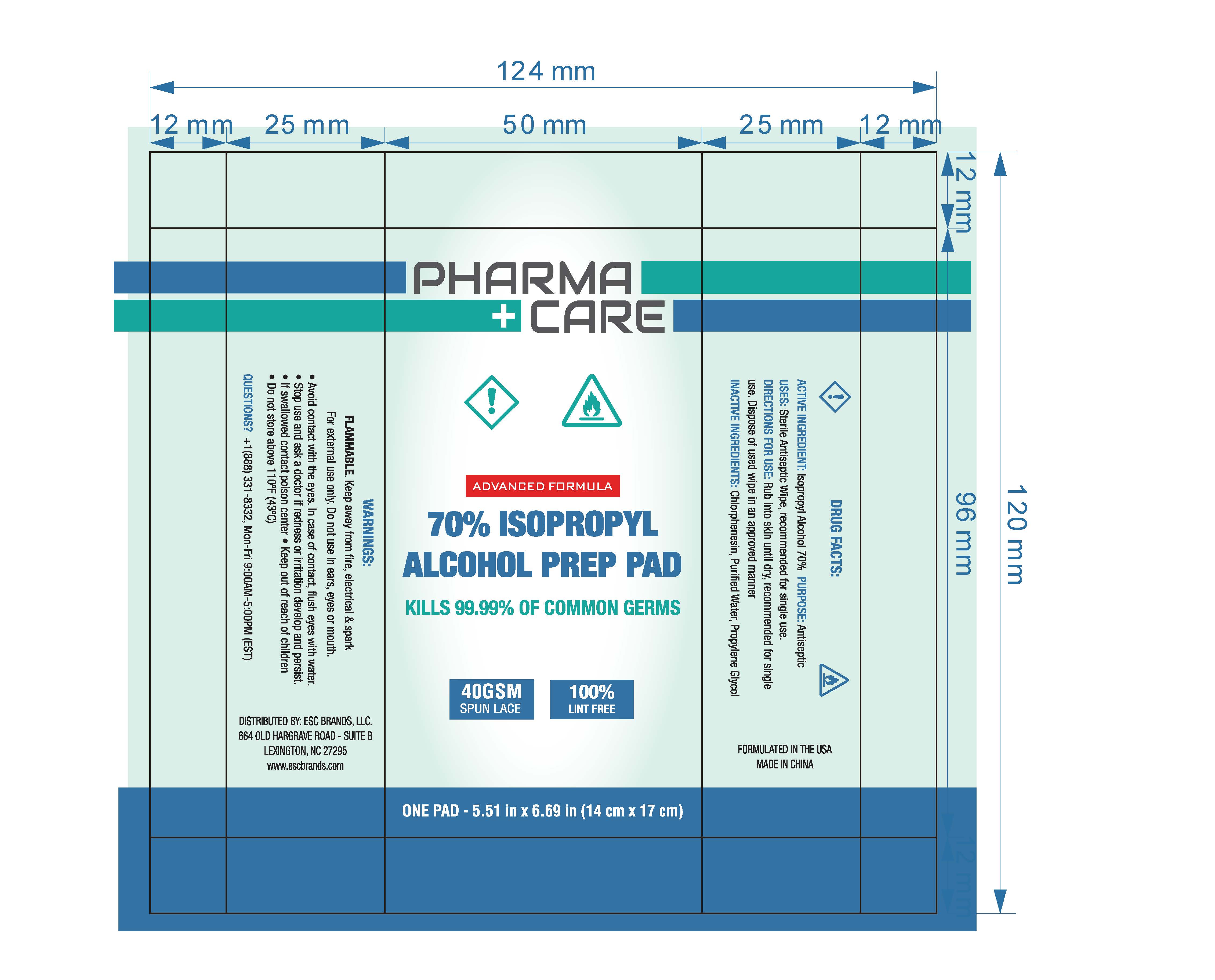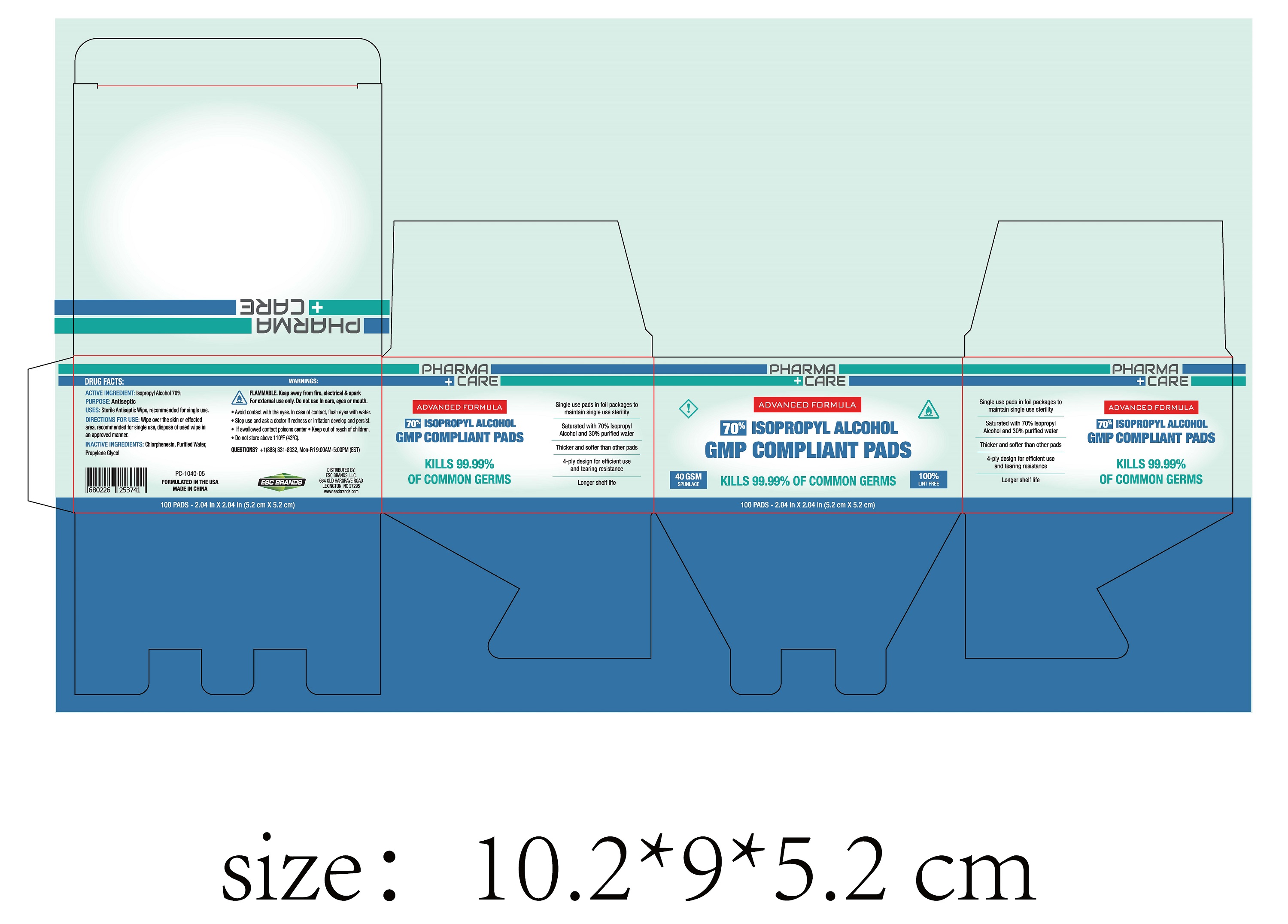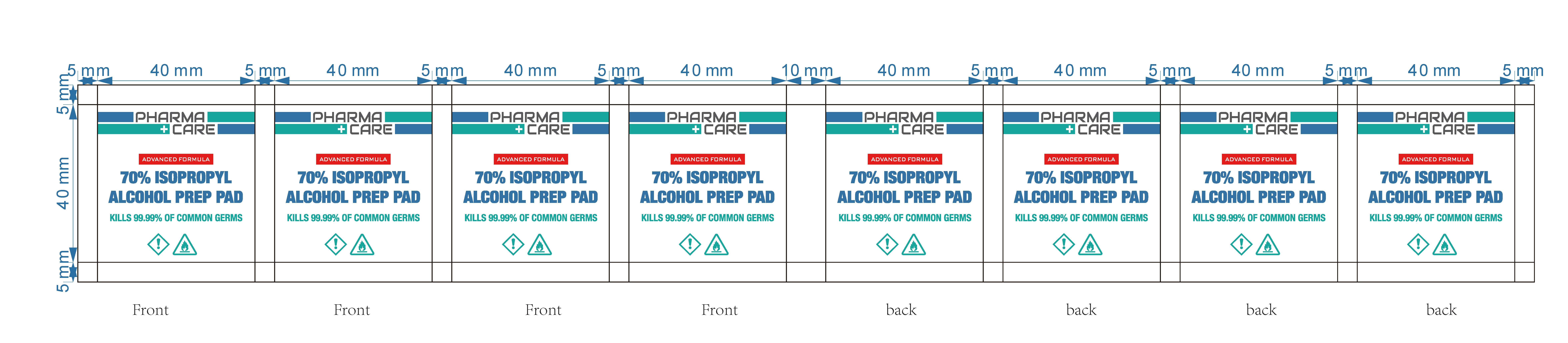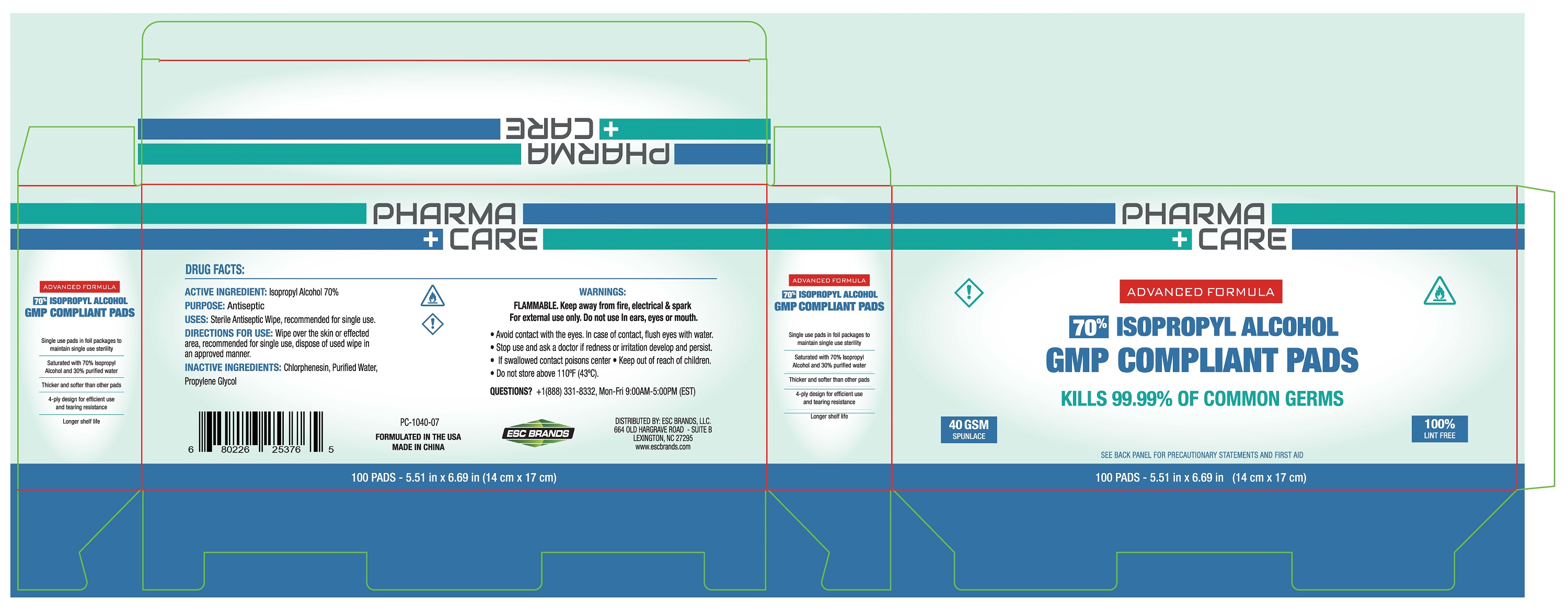 DRUG LABEL: 70% ISOPROPYL ALCOHOL PREP PAD
NDC: 51706-963 | Form: CLOTH
Manufacturer: Landy International
Category: otc | Type: HUMAN OTC DRUG LABEL
Date: 20201230

ACTIVE INGREDIENTS: ISOPROPYL ALCOHOL 70 g/100 g
INACTIVE INGREDIENTS: CHLORPHENESIN; PROPYLENE GLYCOL; WATER

51706-963 70% ISOPROPYL ALCOHOL PREP PAD

Active Ingredient(s)

ACTIVE INGREDIENT: Isopropyl Alcohol 70%

Purpose

Antiseptic

Use

USES: Sterile antiseptic wipe, recommended for single use.

Warnings

FLAMMABLE. Keep away from fire, electrical & spark
For external use only. Do not use In ears, eyes or mouth.
●Avoid contact with the eyes. In case of contact, flush eyes with water
●Stop use and ask a doctor if redness or iritation develop
●If swallowed contact a poison center

Keep out of reach of children.

Directions

Wipe over the skin or affected area, recommended for single use, dispose of used wipe in an approved manner.

Inactive ingredients

INACTIVE INGREDIENTS: Chlorphenesin, Purified Water,
Propylene Glycol